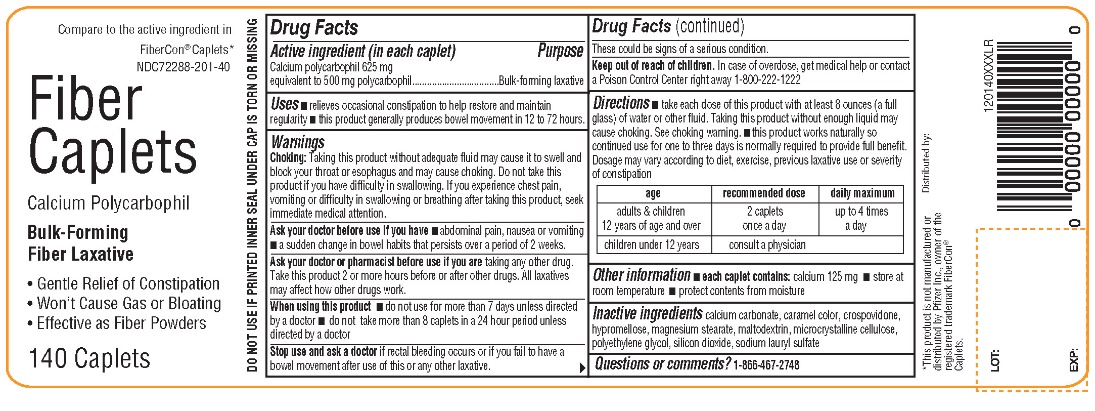 DRUG LABEL: AMAZON
NDC: 72288-201 | Form: TABLET, FILM COATED
Manufacturer: AMAZON.COM SERVICES LLC
Category: otc | Type: HUMAN OTC DRUG LABEL
Date: 20251222

ACTIVE INGREDIENTS: CALCIUM POLYCARBOPHIL 625 mg/1 1
INACTIVE INGREDIENTS: CALCIUM CARBONATE; CARAMEL; CROSPOVIDONE (120 .MU.M); HYPROMELLOSE, UNSPECIFIED; MAGNESIUM STEARATE; MALTODEXTRIN; MICROCRYSTALLINE CELLULOSE; POLYETHYLENE GLYCOL, UNSPECIFIED; SILICON DIOXIDE; SODIUM LAURYL SULFATE

Fiber Caplets Calcium Polycarbophil

Drug Fats

Active Ingredient (in each caplet)

Calcium polycarbophil 625 mg

equivalent to 500 mg polycarbophil

Purpose

Bulk-forming laxative

Uses

- relieves occasional constipation to help restore and maintain regularity
- this product generally produces bowel movement in 12 to 72 hours

WARNINGS

Choking Warning: Taking this product without adequate fluid may cause it to swell and block your throat or esophagus and may cause choking. Do not take this product if you have difficulty in swallowing. If you experience chest pain, vomiting, or difficulty in swallowing or breathing after taking this product, seek immediate medical attention.

Ask a doctor before use if you have

- abdominal pain, nausea, or vomiting
- a sudden change in bowel habits that persists over a period of 2 weeks

Ask your doctor or pharmacist before use if you are

taking any other drug. Take this product 2 or more hours before or after other drugs. All laxatives may affect how other drugs work.

When using this product

- do not use for more than 7 days unless directed by a doctor
- do not take more than 8 caplets in a 24 hour period unless directed by a doctor

Stop use and ask a doctor if

rectal bleeding occurs or if you fail to have a bowel movement after use of this or any other laxative. These could be signs of a serious condition.

Keep out of reach of children.

OVERDOSAGE

In case of overdose, get medical help or contact a Poison Control Center right away at 1-800-222-1222.

Directions

- take each dose of this product with at least 8 ounces (a full glass) of water or other fluid. Taking this product without enough liquid may cause choking. (See choking warning).
- this product works naturally so continued use for one to three days is normally required to provide full benefit. Dosage may vary according to diet, exercise, previous laxative use or severity of constipation.

age | Recommended dose | Daily maximum
adults & children 12 years of age and over | 2 caplets once a day | up to 4 times a day
children under 12 years | consult a physician

Other information

- each caplet contains: calcium 125 mg
- store at room temperature
- protect contents from moisture

DO NOT USE IF PRINTED SEAL UNDER CAP IS TORN OR MISSING

INACTIVE INGREDIENT

calcium carbonate, caramel color, crospovidone, hypromellose, magnesium stearate, maltodextrin, microcrystalline cellulose, polyethylene glycol, silicon dioxide, sodium lauryl sulfate.

Questions or Comments?

1-866-467-2748

PRINCIPAL DISPLAY PANEL

NDC# 21130-021-40

*Compare to the active ingredients of Fibercon® Caplets*

NDC 72288-201-40

Fiber Caplets

Calcium Polycarbophil

Bulk-Forming

Fiber Laxative

- Gentle Relief of Constipation
- Won’t Cause Gas or Bloating
- Effective as Fiber Powders

140 Caplets

Distributed by:

*This product is not manufactured or distributed by Pfizer Inc., owner of the registered trademark Fibercon® Caplets.